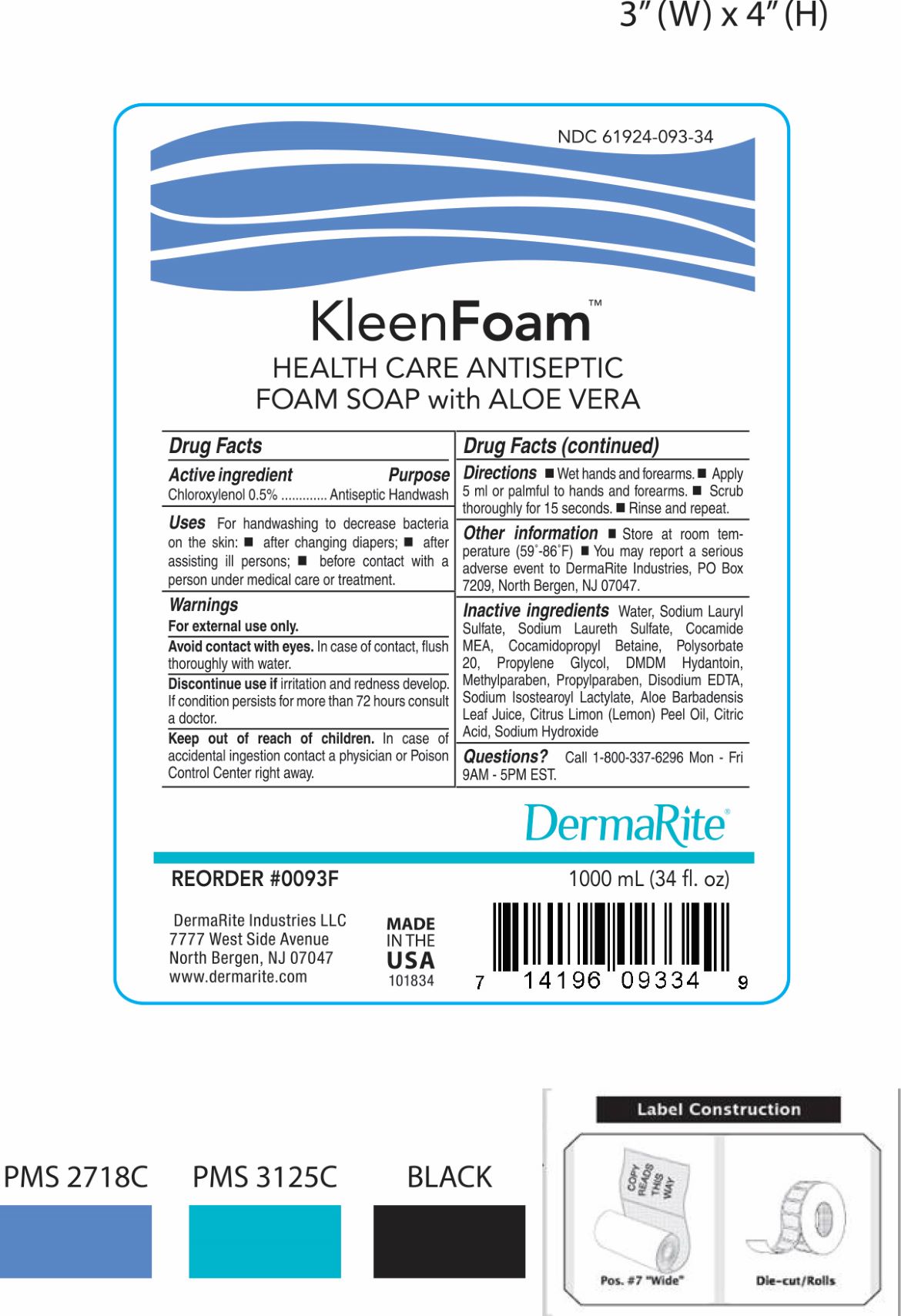 DRUG LABEL: KLEENFOAM
NDC: 61924-093 | Form: AEROSOL, FOAM
Manufacturer: Dermarite Industries LLC
Category: otc | Type: HUMAN OTC DRUG LABEL
Date: 20241205

ACTIVE INGREDIENTS: CHLOROXYLENOL 0.005 g/1 mL
INACTIVE INGREDIENTS: SODIUM LAURYL SULFATE; PROPYLENE GLYCOL; DMDM HYDANTOIN; METHYLPARABEN; PROPYLPARABEN; EDETATE SODIUM; SODIUM HYDROXIDE; SODIUM CHLORIDE; LEMON OIL; POLYSORBATE 20; SODIUM ISOSTEAROYL LACTYLATE; WATER; ALOE VERA LEAF; CITRIC ACID MONOHYDRATE; COCO MONOETHANOLAMIDE; COCAMIDOPROPYL BETAINE; METHYLCHLOROISOTHIAZOLINONE; METHYLISOTHIAZOLINONE; SODIUM LAURETH SULFATE

DRUG LISTING: KLEENFOAM

Active Ingredient

Chloroxylenol 0.5%

Purpose:

Antiseptic Handwash

Uses:

- For handwashing to decrease bacteria on the skin.
- after changing diapers;
- after assisting ill persons;
- before contact with a person under medical care or treatmentRecommended for repeated use.

Warnings:

- For external use only.
- Avoid contact with eyes. In case of contact, flush thoroughly with water.
- Ask a doctor before use if you have , deep of puncture wounds, animal bites, serious burns
- When using this product, do not apply to areas of raw or blistered skin in large quantities, do not use in or near the eyes
- Stop use and ask a doctor if, condition worsens, symptoms last for more than 7 days or clear up and recur within a few days

Warnings:

For external use only.

Avoid contact with eyes. In case of contact, flush thoroughly with water.

Discontinue use if irritation and redness develop. If condition persists for more than 72 hours consult a doctor.

Keep out of reach of children. In case of accidental ingestion contact a physician or Poison Control Center right away

Directions:

- Wet hands and forearms.
- Apply 5 millimeters (teaspoon) or palmful to hands and forearms.
- Scrub thoroughly for 15 seconds.
- Rinse and repeat.

Other information:

Store at room temperature (59°-86°F). You may report a serious adverse event to DermaRite Industries, PO Box 7209, North Bergen, NJ 07047

Inactive Ingredients:

Water, Sodium Lauryl sulfate, Sodium Laureth Sulfate, Cocamide MEA, Cocamidopropyl Betaine, Polysorbate 20, Propylene Glycol, DMDM Hydantoin, Methylparaben, Propylparaben, Disodium EDTA, Sodium Isostearoyl lactylate, Aloe Barbadensis Leaf Juice, Citrus Limon (Lemon) Peel Oil, Citric Acid, Sodium Hydroxide

Question?

Call 1-800-337-6296 Mon-Fri 9AM-5PM EST.